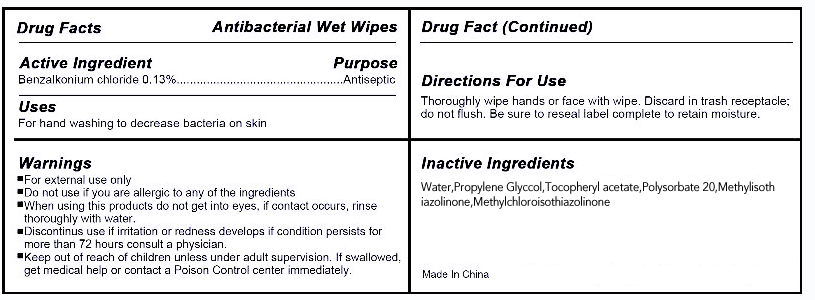 DRUG LABEL: Antibacterial Wet Wipes
NDC: 73015-001 | Form: SWAB
Manufacturer: HangZhou YangYi Daily Cosmetics Technology Co., Ltd.
Category: otc | Type: HUMAN OTC DRUG LABEL
Date: 20231213

ACTIVE INGREDIENTS: BENZALKONIUM CHLORIDE 0.13 g/100 g
INACTIVE INGREDIENTS: WATER; PROPYLENE GLYCOL; TOCOPHERYL RETINOATE; POLYSORBATE 20; METHYLISOTHIAZOLINONE; METHYLCHLOROISOTHIAZOLINONE

Antibacterial Wet Wipes

Active ingredient

benzalkonium chloride 0.13%

Purpose

Antibacterial

Uses

for hand washing to decrease bacteria on skin

Warnings

For External use only.
Do not use if you are allergic to any of the ingredients.
When using this product Do not get into eyes,if contact occurs ,rinse throughly with water.
Discontinue use if irritation or redness develops if condition persists for more than 72 hours consults a physician.

keep out of reach of children unless under adult supervision .if seallowed ,get medical help or contact a Poison Control Center immediately.

Directions

Thoroughly wipe hands or face with wipe,Discard in trash receptacle;do not flush.Be sure to reseal label complete to retain moisture

INACTIVE INGREDIENT

WATER PROPYLENE GLYCOL OCTHILINONE .ALPHA.-TOCOPHEROL